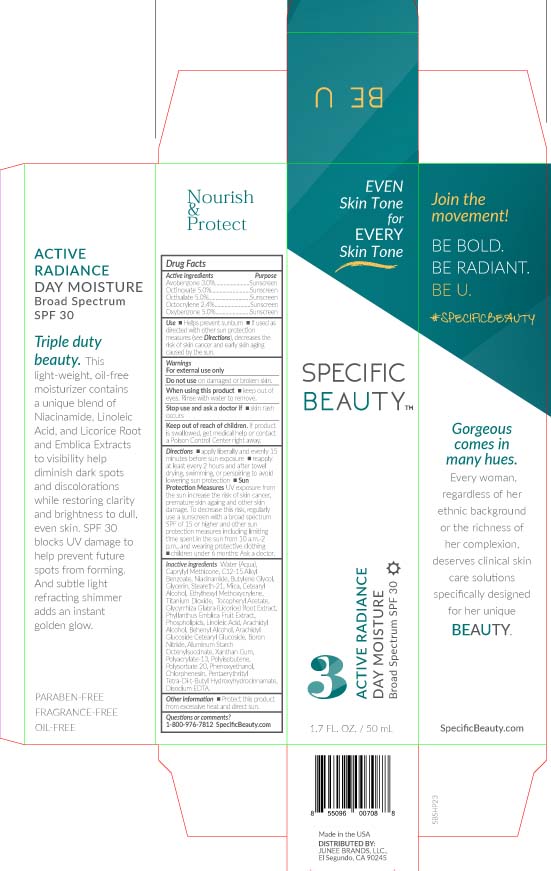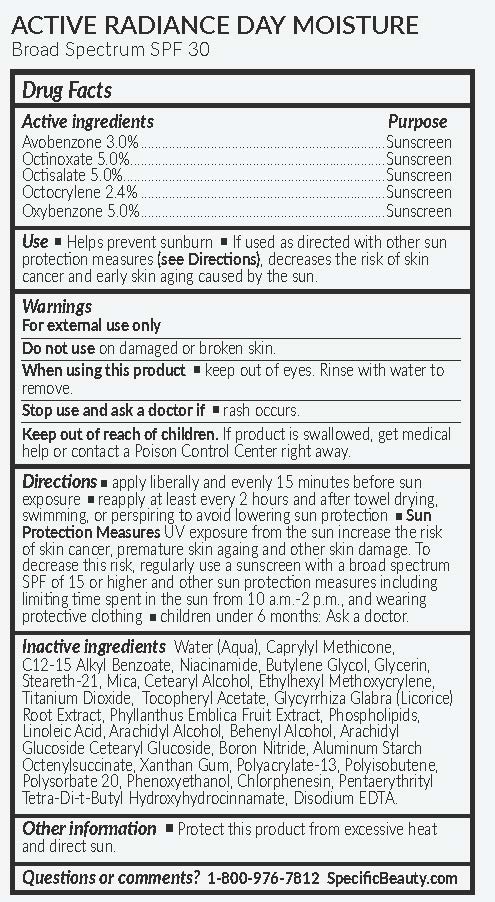 DRUG LABEL: Active Radiance Day Moisture SPF 30
NDC: 56152-5004 | Form: CREAM
Manufacturer: COSMETIC ENTERPRISES LTD
Category: otc | Type: HUMAN OTC DRUG LABEL
Date: 20241113

ACTIVE INGREDIENTS: AVOBENZONE 3 g/100 mL; OCTINOXATE 5 g/100 mL; OCTISALATE 5 g/100 mL; OCTOCRYLENE 2.4 g/100 mL; OXYBENZONE 5 g/100 mL
INACTIVE INGREDIENTS: WATER; CAPRYLYL TRISILOXANE; ALKYL (C12-15) BENZOATE; NIACINAMIDE; BUTYLENE GLYCOL; GLYCERIN; STEARETH-21; MICA; CETOSTEARYL ALCOHOL; ETHYLHEXYL METHOXYCRYLENE; TITANIUM DIOXIDE; .ALPHA.-TOCOPHEROL ACETATE; GLYCYRRHIZA GLABRA; LINOLEIC ACID; ARACHIDYL ALCOHOL; DOCOSANOL; ARACHIDYL GLUCOSIDE; CETEARYL GLUCOSIDE; BORON NITRIDE; ALUMINUM STARCH OCTENYLSUCCINATE; XANTHAN GUM; POLYISOBUTYLENE (1000 MW); POLYSORBATE 20; PHENOXYETHANOL; CHLORPHENESIN; PENTAERYTHRITOL TETRAKIS(3-(3,5-DI-TERT-BUTYL-4-HYDROXYPHENYL)PROPIONATE); EDETATE DISODIUM

Active Radiance Day Moisture Broad Spectrum SPF 30

Active Ingredients Purpose

Avobenzone 3.0% ........................ Sunscreen

Octinoxate 5.0% ........................... Sunscreen

Octisalate 5.0% ............................ Sunscreen

Octocrylene 2.4% ......................... Sunscreen

Oxybenzone 5.0% ........................ Sunscreen

Uses

- Helps prevent sunburn
- If used as directed with other sun protection measures (see Directions), decreases the risk of skin Cancer and early skin aging cause by the sun

Keep out of reach of children.If product is swallowed, get medical help or contact a Poison Control Center right away

Stop use and ask a doctor if- rash occurs

Warnings

- For exter use only
- Do not useon damaged or broken skin
- when usign this porductkeep out of eyes. Rinse with water to remove

Directions

- apply liberally and evenly 15 minutes before sun exposure
- reapply at least every 2 hours and after towel drying, swimming, or perspiring to avoid lowering sun protection
- Sun Protection MeasuresUV exposure from the sun increase to the risk of skin cancer, premature skin aging and other skin damage. To decrease this risk, regularly use a sunscreen with a broad spectrum SPF of 15 or higher and other sun protection measures including limiting time spent in the sun from 10 a.m. - 2 p.m. and wearing protective clothing
- Children under 6 months: Ask a doctor

INACTIVE INGREDIENT

Water (Aqua), Caprylyl Methicone, C12-15 Alkyl Benzoate, Niacinamide, Butylene Glycol, Glycerin, Steareth-21, Mica, Cetearyl Alcohol, Ethylhexyl Methoxycrylene, Titanium Dioxide, Tocopheryl Acetate, Glycyrrhiza Glabra (Licorice) Root Extract, Phyllanthus Emblica Fruit Extract, Phospholipids, Linoleic Acid, Arachidly Alcohol, Behenyl Alcohol, Arachidyl Glucoside, Cetearyl Glucoside, Boron Nitride, Aluminum Starch Octenylsuccinate, Xanthan Gum, Polyacrylate-13, Polyisobutene, Polysorbate 20, Phenoxyethanol, Chlorphenesin, Pentaerythrityl Tetra-Di-t-Buty Hydroxyhydrocinnamate, Disodium EDTA

PACKAGE LABEL

Specific Beauty

Active Radiance

Day Moisture

Broad Spectrum SPF 30

1.7 FL. OZ. / 50 mL